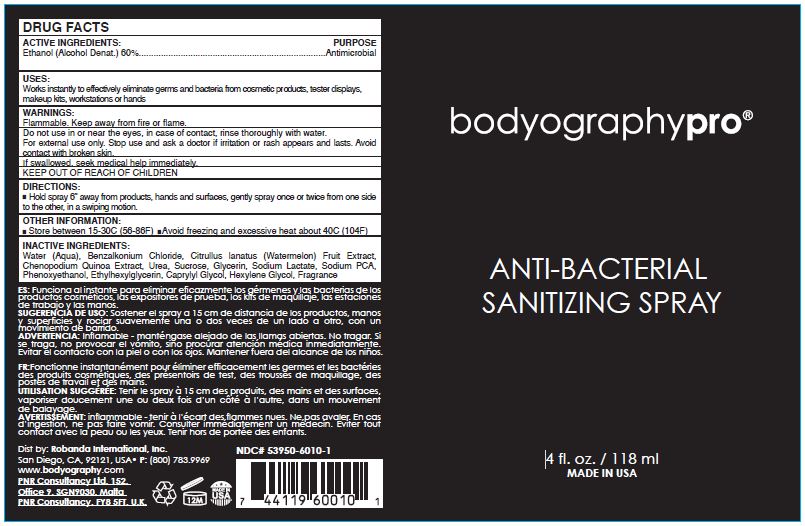 DRUG LABEL: BODYOGRAPHYPRO ANTI-BACTERIAL SANITIZING
NDC: 53950-6010 | Form: SPRAY
Manufacturer: Robanda International, Inc.
Category: otc | Type: HUMAN OTC DRUG LABEL
Date: 20250108

ACTIVE INGREDIENTS: ALCOHOL 60 mL/100 mL
INACTIVE INGREDIENTS: BENZALKONIUM CHLORIDE; WATER; WATERMELON; CHENOPODIUM QUINOA SEED; UREA; SUCROSE; GLYCERIN; SODIUM LACTATE; SODIUM PYRROLIDONE CARBOXYLATE; PHENOXYETHANOL; ETHYLHEXYLGLYCERIN; CAPRYLYL GLYCOL; HEXYLENE GLYCOL

Robanda International BODYOGRAPHYPRO ANTI-BACTERIAL SANITIZING SPRAY (53950-6010)

Active ingredient

ETHANOL (Alcohol Denat.) 60.00%

Purpose

Antimicrobial

uses

Works instantly to effectively eliminate germs and bacteria from cosmetic products, tester displays, makeup kits, workstations or hands

Warnings

Flammable. Keep away from fire or flame.
Do not use in or near the eyes, in case of contact, rinse thoroughly with water.
For external use only. Stop use and ask a doctor if irritation or rash appears and lasts. Avoid contact with broken skin.

If swallowed, seek medical help immediately.

KEEP OUT OF REACH OF CHILDREN

Directions

- Hold spray 6” away from products, hands and surfaces, gently spray once or twice from one side to the other, in a swiping motion.

OTHER INFORMATION

- Store between 15-30C (56-86F)
- Avoid freezing and excessive heat about 40C (104F)

Inactive ingredients

Water (aqua), Citrullus lanatus (Watermelon) Fruit Extract, Chenopodium quinoa Extract, Urea, Sucrose, Glycerin, Sodium Lactate, Sodium
PCA, Phenoxyethanol, Ethylhexylglycerin, Caprylyl Glycol, Hexylene Glycol, Fragrance